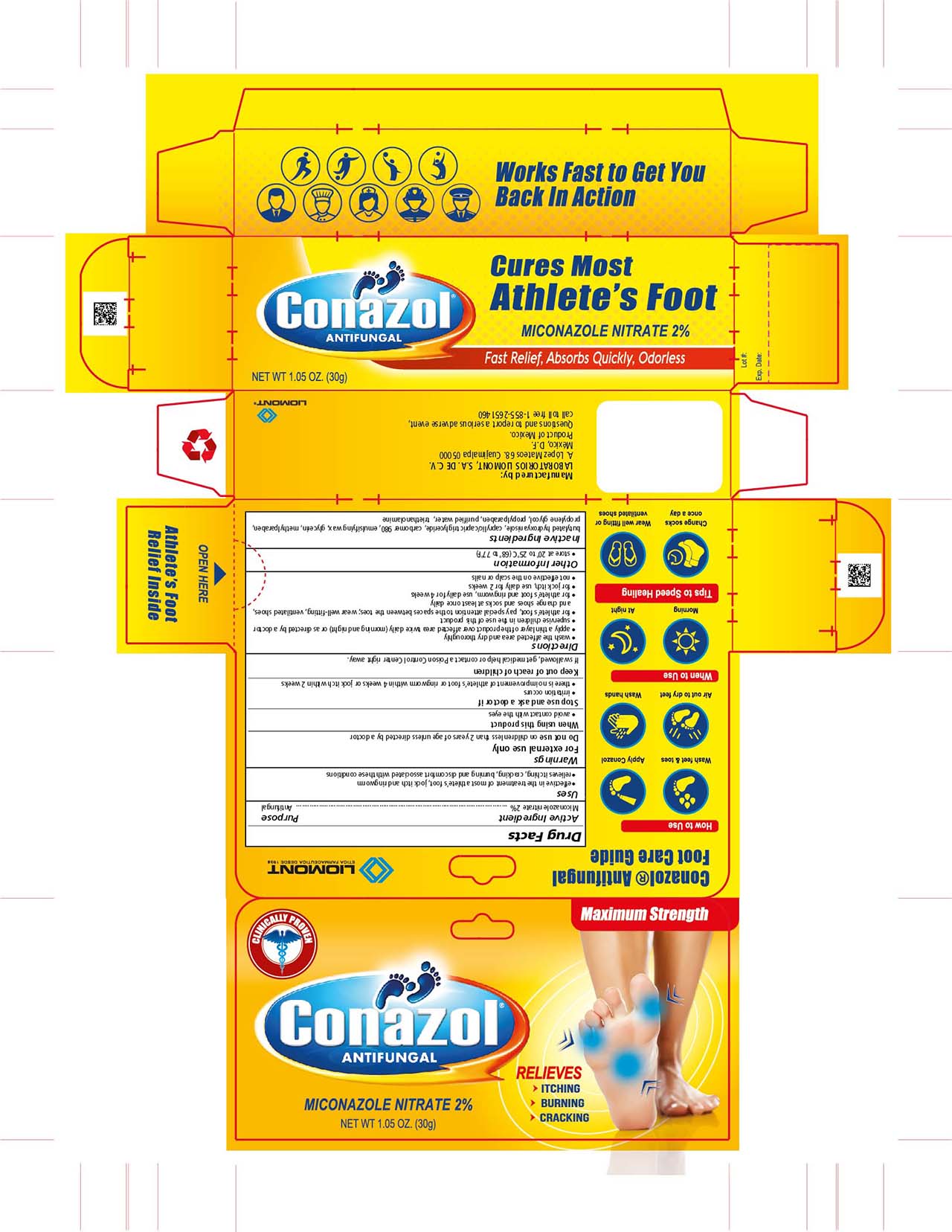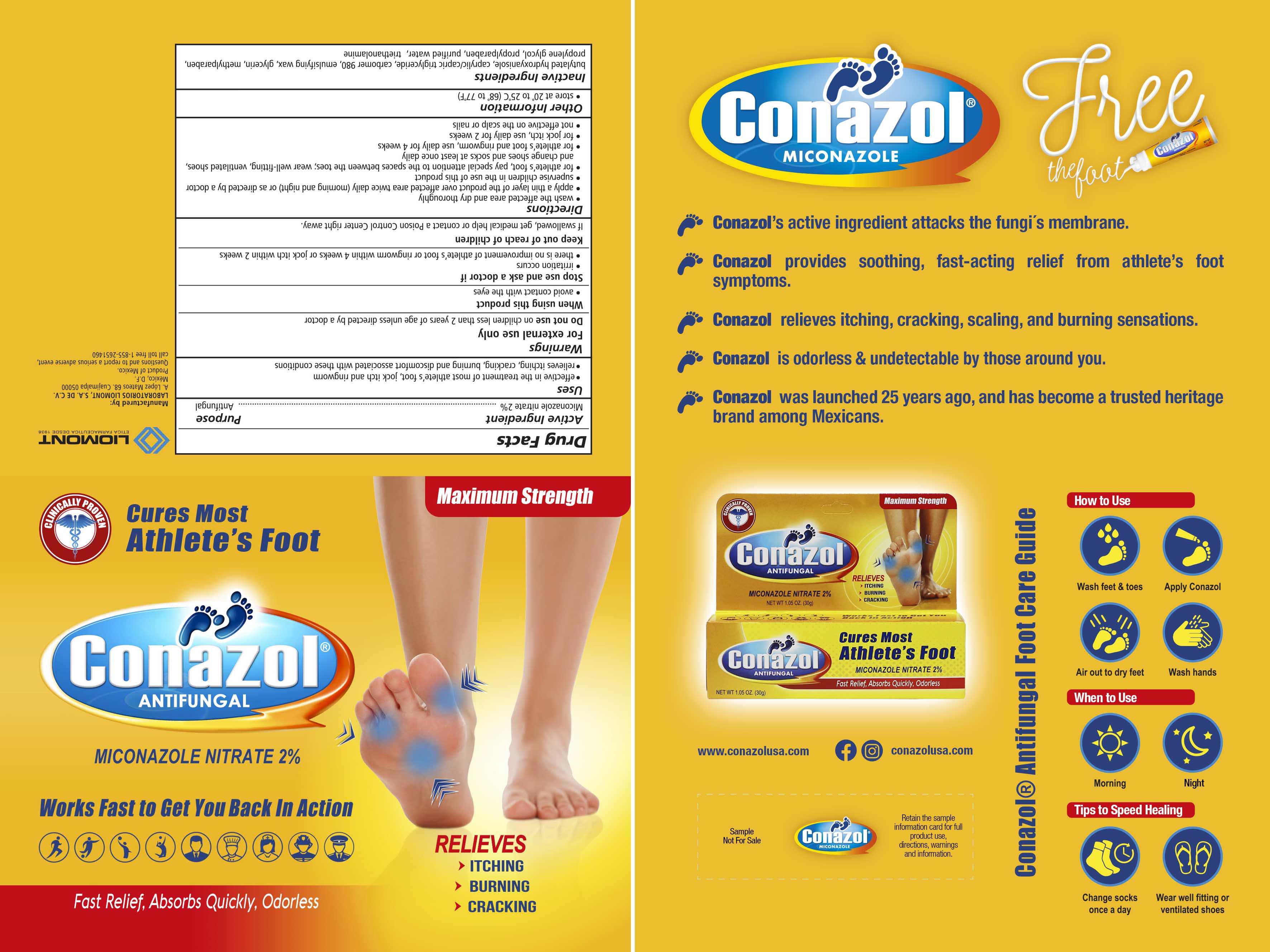 DRUG LABEL: Conazol
NDC: 59208-001 | Form: CREAM
Manufacturer: Laboratorios Liomont, S.A. de C.V.
Category: otc | Type: HUMAN OTC DRUG LABEL
Date: 20250707

ACTIVE INGREDIENTS: MICONAZOLE NITRATE 20 mg/1 g
INACTIVE INGREDIENTS: BUTYLATED HYDROXYANISOLE; MEDIUM-CHAIN TRIGLYCERIDES; CARBOMER HOMOPOLYMER TYPE C (ALLYL PENTAERYTHRITOL CROSSLINKED); GLYCERIN; METHYLPARABEN; PROPYLENE GLYCOL; PROPYLPARABEN; WATER; TROLAMINE

Conazol Cream

Active Ingredient

Miconazole nitrate 2%

Purpose

Antifungal

Uses

- effective in the treatment of most athlete's foot, jock itch and ringworm
- relieves itching, cracking, burning and discomfort associated with these conditions

Warnings

For external use only

Do not use

on children less than 2 years of age unless directed by a doctor

When using this product

• avoid contact with the eyes

Stop use and ask a doctor if

- irritation occurs
- there is no improvement of athlete's foot or ringworm within 4 weeks or jock itch within 2 weeks

Keep out of reach of children

If swallowed, get medical help or contact a Poison Control Center right away.

Directions

- wash the affected area and dry thoroughly
- apply a thin layer of the product over affected area twice daily (morning and night) or as directed by a doctor
- supervise children in the use of this product
- for athlete's foot, pay special attention to the spaces between the toes; wear well-fitting, ventilated shoes,and change shoes

and socks at least once daily

- for the athlete's foot and ringworm, use daily for 4 weeks
- for jock itch, use daily for 2 weeks
- not effective on the scalp or nails

Other Information

- store at 20° to 25°C (68° to 77°F)

Inactive Ingredients

butylated hydroxyanisole, caprylic/capic triglyceride,carbomer 980, emulsifying wax, glycerin, methylparaben, propylene glycol, propylparaben, purified water, triethanolamine